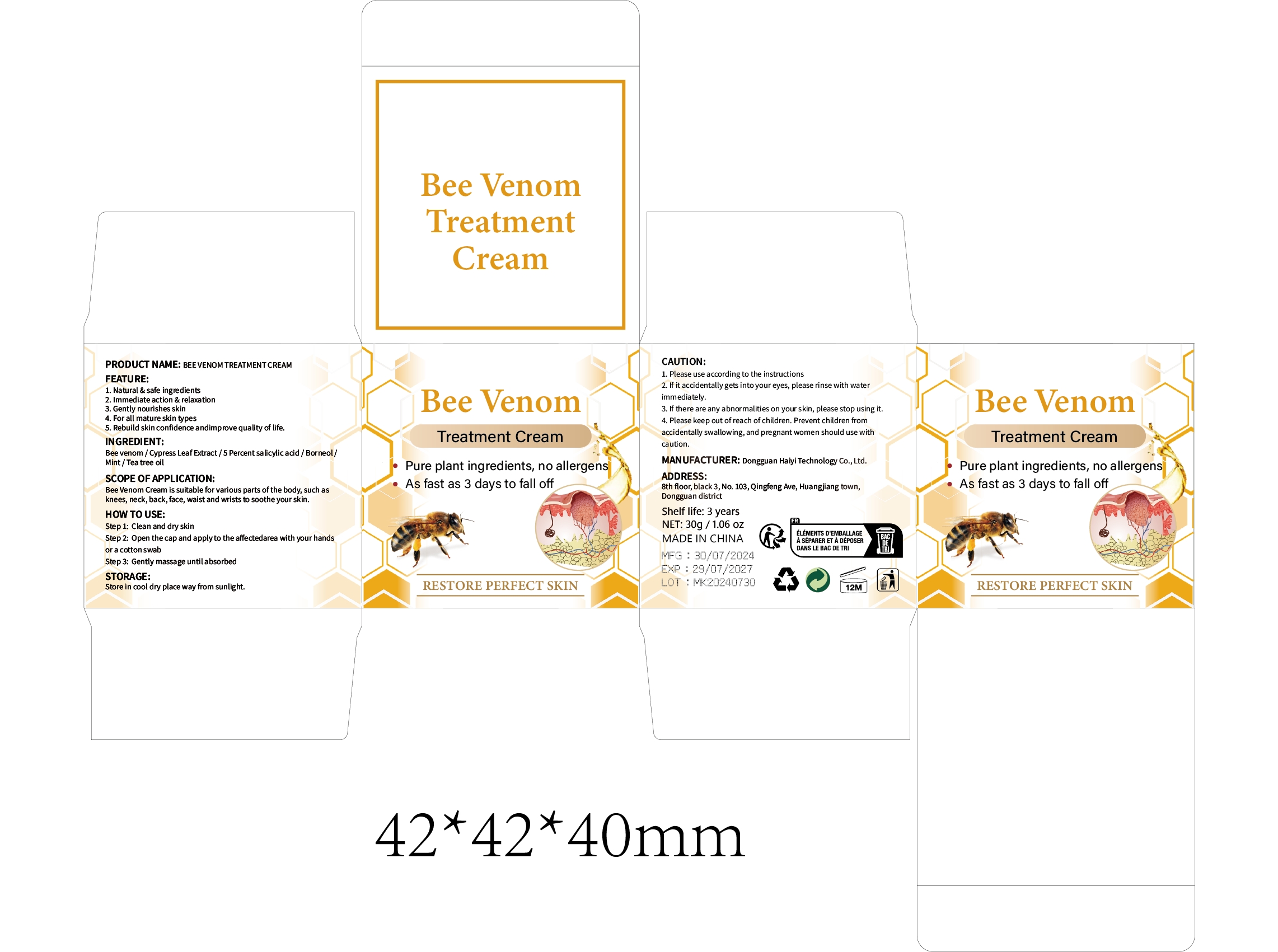 DRUG LABEL: BEE VENOM TREATMENT Cream
NDC: 84732-065 | Form: CREAM
Manufacturer: Dongguan Haiyi Technology Co.,Ltd.
Category: otc | Type: HUMAN OTC DRUG LABEL
Date: 20241025

ACTIVE INGREDIENTS: APIS MELLIFERA VENOM 1 mg/100 g
INACTIVE INGREDIENTS: TEA TREE OIL; CUPRESSUS SEMPERVIRENS LEAF; SALICYLIC ACID; MINT; BORNEOL

Active ingredient

Bee venom

Inactive ingredient

Cypress Leaf Extract /5 Percent salicylic acid / Borneol/Mint / Tea tree oil

Purpose section

1. Natural & safe ingredients

2. lmmediate action & relaxation

3. Gently nourishes skin
4. For all mature skin types

5. Rebuild skin confidence andimprove quality of life,

Warning

1. Please use according to the instructions

2. if it accidentally gets into your eyes, please rinse with waterimmediately.
3. lf there are any abnormalities on your skin, please stop using it.

4. Please keep out of reach of children. Prevent children fromaccidentally swallowing, and pregnant women should use withcaution.

stop use

This product may cause allergic reactions in asmall number of people.
lf youexperience any discomfort,please stop using it immediately.

not use

Not suitable for use by children, pregnantor breast feeding people.

OUT OF CHILDREN

KEEP THE PRODUCT OUT OF REACH OF CHILDREN to

HOW TO USE

Step 1: Clean and dry skin
Step 2: Open the cap and applyto the affectedarea with your handsor a cotton swab
Step 3: Gently massage until absorbed

DOSAGE

As fast as 3 days to fall off